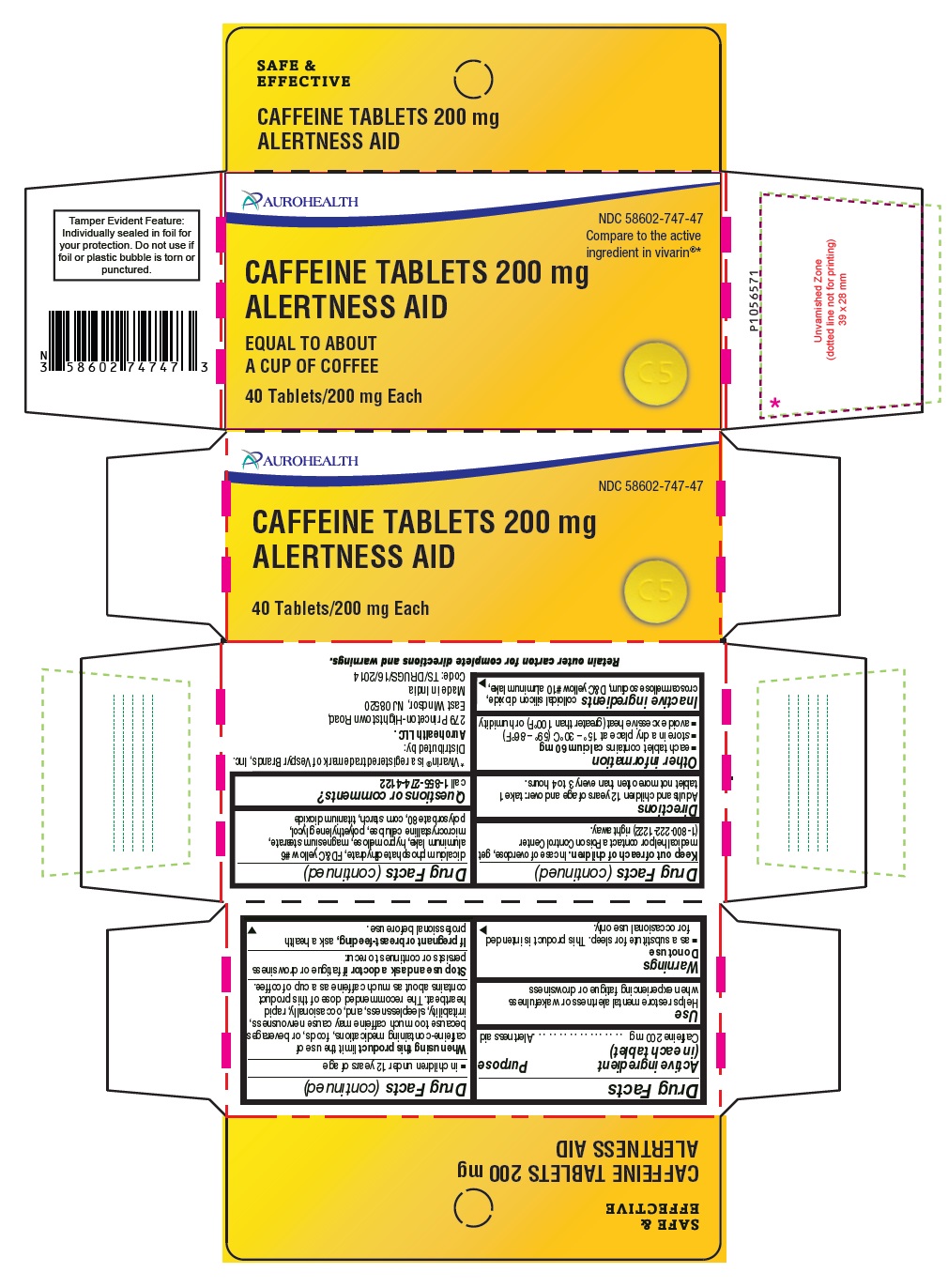 DRUG LABEL: caffeine
NDC: 58602-747 | Form: TABLET
Manufacturer: Aurohealth LLC
Category: otc | Type: Human OTC Drug Label
Date: 20240920

ACTIVE INGREDIENTS: CAFFEINE 200 mg/1 1
INACTIVE INGREDIENTS: SILICON DIOXIDE; CROSCARMELLOSE SODIUM; D&C YELLOW NO. 10 ALUMINUM LAKE; DIBASIC CALCIUM PHOSPHATE DIHYDRATE; FD&C YELLOW NO. 6; HYPROMELLOSE, UNSPECIFIED; MAGNESIUM STEARATE; MICROCRYSTALLINE CELLULOSE; POLYETHYLENE GLYCOL, UNSPECIFIED; POLYSORBATE 80; STARCH, CORN; TITANIUM DIOXIDE

Drug Facts

Active ingredient (in each tablet)

Caffeine 200mg

Purpose

Alertness aid

Use

Helps restore mental alertness or wakefulness when experiencing fatigue or drowsiness

Warnings

Do not use

- as a substitute for sleep. This product is intended for occasional use only.
- in children under 12 years of age

When using this product

limit the use of caffeine-containing medications, foods, or beverages because too much caffeine may cause nervousness, irritability, sleeplessness, and, occasionally, rapid heartbeat. The recommended dose of this product contains about as much caffeine as a cup of coffee.

Stop use and ask a doctor if

fatigue or drowsiness persists or continues to recur.

If pregnant or breast-feeding,

ask a health professional before use.

Keep out of reach of children.

In case of overdose, get medical help or contact a Poison Control Center (1-800-222-1222) right away.

Directions

Adults and children 12 years of age and over: take 1 tablet not more often than every 3 to 4 hours.

Other information

- each tablet contains calcium 60 mg
- store in a dry place at 15° - 30°C (59° - 86°F)
- avoid excessive heat (greater than 100°F) or humidity

Inactive ingredients

colloidal silicon dioxide, croscarmellose sodium, D&C yellow #10 aluminum lake, dicalcium phosphate dihydrate, FD&C yellow #6 aluminum lake, hypromellose, magnesium stearate, microcrystalline cellulose, polyethylene glycol, polysorbate 80, corn starch, titanium dioxide

Questions or comments?

Call 1-855-274-4122
Distributed by:
Aurohealth LLC.
279 Princeton-Hightstown Road,
East Windsor, NJ 08520
Made in India
Code: TS/DRUGS/16/2014

PACKAGE LABEL-PRINCIPAL DISPLAY PANEL 200 mg (40 Tablets Blister Carton)

AUROHEALTH
NDC 58602-747-47
Compare to the active
ingredient in Vivarin®*
CAFFEINE TABLETS 200 mg
ALERTNESS AID
EQUAL TO ABOUT
A CUP OF COFFEE
40 Tablets/200 mg Each